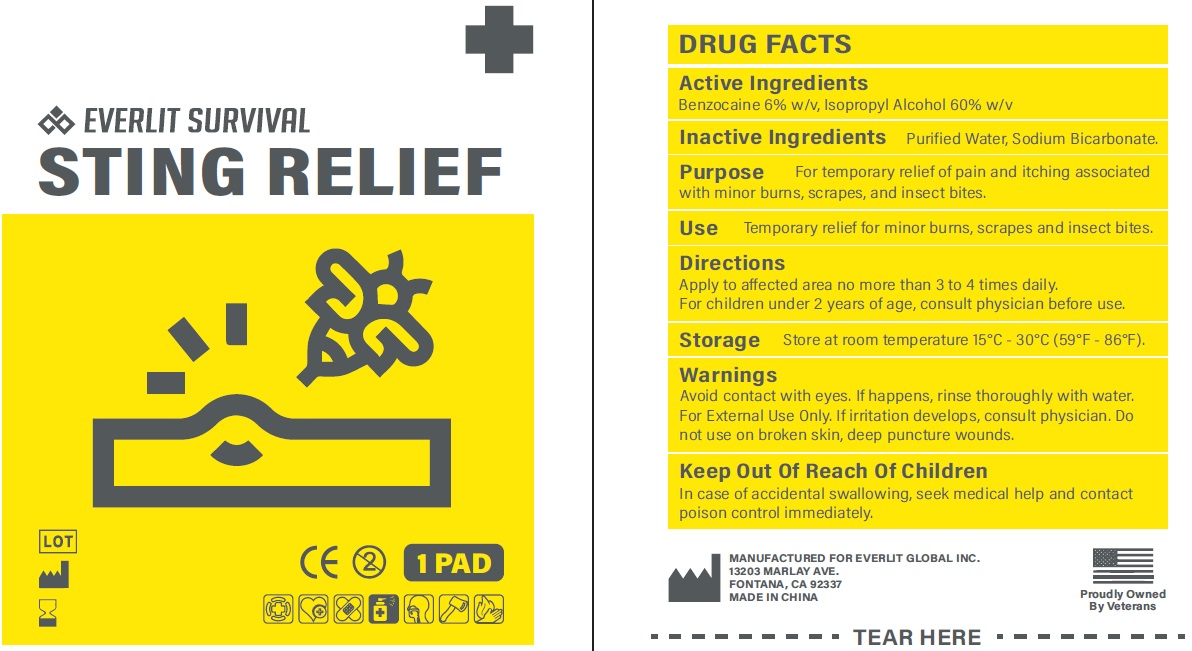 DRUG LABEL: Sting Relief
NDC: 72459-016 | Form: SOLUTION
Manufacturer: Yiwu Ori-Power Medtech Co.,Ltd.
Category: otc | Type: HUMAN OTC DRUG LABEL
Date: 20260101

ACTIVE INGREDIENTS: BENZOCAINE 60 mg/1 g; ISOPROPYL ALCOHOL 600 mg/1 g
INACTIVE INGREDIENTS: WATER; SODIUM BICARBONATE

EVERLIT SURVIVAL Sting Relief

Active Ingredients

Benzocaine 6% w/v, Isopropyl Alcohol 60% w/v

Purpose

For temporary relief of pain and itching associated with minor burns, scrapes, and insect bites.

Inactive Ingredients

Purified Water, Sodium Bicarbonate.

Use

Temporary relief for minor burns, scrapes and insect bites.

Directions

Apply to affected area no more than 3 to 4 times daily. For children under 2 years of age, consult physician before use.

Storage

Store at room temperature 15°C - 30°C (59°F - 86°F).

Warnings

Avoid contact with eyes. If happens, rinse thoroughly with water. For External Use Only. If irritation develops, consult physician. Do not use on broken skin, deep puncture wounds.

Keep Out Of Reach Of Children

In case of accidental swallowing, seek medical help and contact poison control immediately.

Do not use

on broken skin, deep puncture wounds.